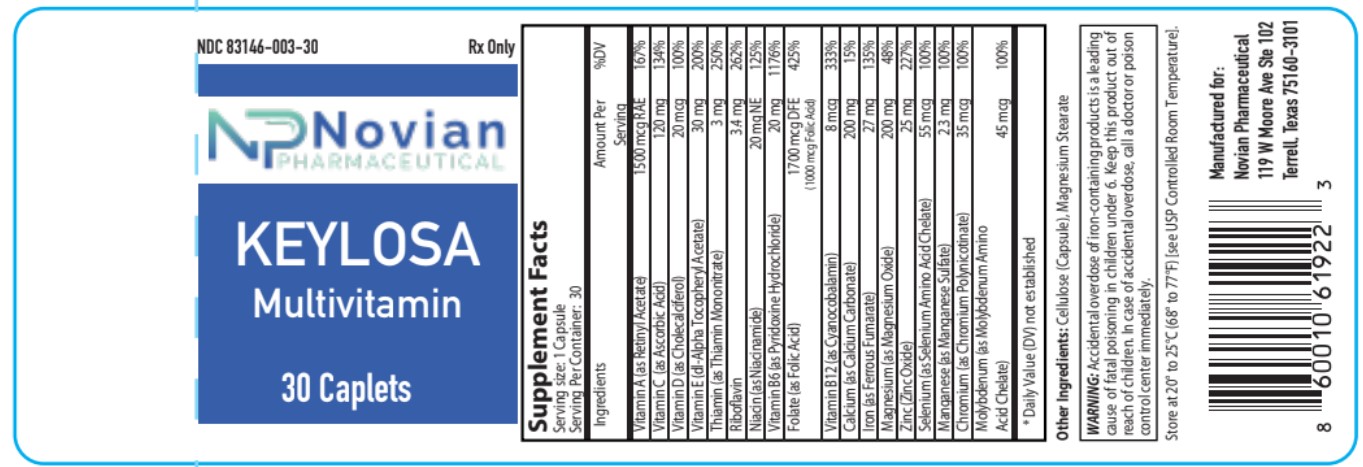 DRUG LABEL: Keylosa
NDC: 83146-003 | Form: CAPSULE, COATED
Manufacturer: Novian Pharmaceuticals
Category: prescription | Type: HUMAN PRESCRIPTION DRUG LABEL
Date: 20231006

ACTIVE INGREDIENTS: CHOLECALCIFEROL 20 ug/1 1; FOLIC ACID 1000 ug/1 1; MANGANESE SULFATE 23 mg/1 1; VITAMIN A 1500 ug/1 1; ASCORBIC ACID 120 mg/1 1; PYRIDOXINE 20 mg/1 1; CHROMIUM 35 ug/1 1; RIBOFLAVIN 3.4 mg/1 1; MAGNESIUM OXIDE 200 mg/1 1; SELENIUM 55 ug/1 1; MOLYBDENUM 45 ug/1 1; ZINC OXIDE 25 mg/1 1; CYANOCOBALAMIN 8 ug/1 1; FERROUS FUMARATE 27 mg/1 1; .ALPHA.-TOCOPHEROL 30 mg/1 1; THIAMINE MONONITRATE 3 mg/1 1; NIACINAMIDE 20 mg/1 1; CALCIUM CARBONATE 200 mg/1 1
INACTIVE INGREDIENTS: MAGNESIUM STEARATE

Keylosa

WARNINGS

Accidental overdose of iron-containing products is a leading cause of fatal poisoning in children under 6. Keep this product out of
reach of children. In case of accidental overdose, call a doctor or poison control.

STORAGE AND HANDLING

Store at 20° to 25°C (68° to 77°F) [see USP Controlled Room Temperature].

INACTIVE INGREDIENT

Other Ingredients: Cellulose (capsule), Magnesium Stearate